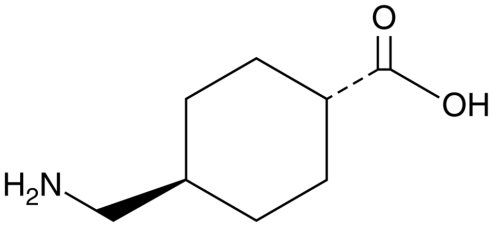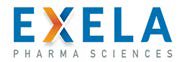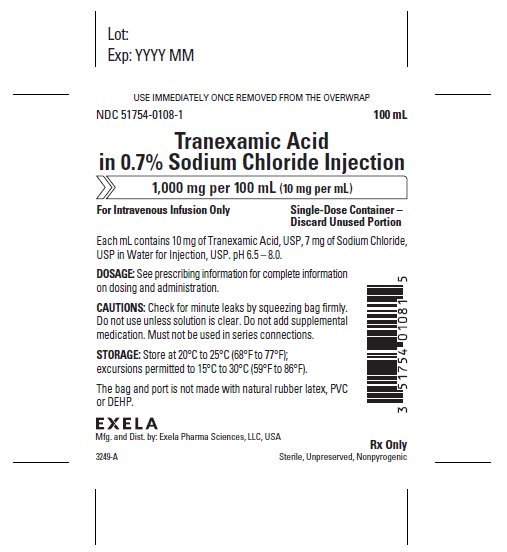 DRUG LABEL: TRANEXAMIC ACID IN SODIUM CHLORIDE
NDC: 51754-0108 | Form: INJECTION, SOLUTION
Manufacturer: Exela Pharma Sciences, LLC
Category: prescription | Type: HUMAN PRESCRIPTION DRUG LABEL
Date: 20190422

ACTIVE INGREDIENTS: TRANEXAMIC ACID 10 mg/1 mL
INACTIVE INGREDIENTS: SODIUM CHLORIDE; WATER

HIGHLIGHTS OF PRESCRIBING INFORMATION

These highlights do not include all the information needed to use TRANEXAMIC ACID IN SODIUM CHLORIDE INJECTION safely and effectively. See full prescribing information for TRANEXAMIC ACID IN SODIUM CHLORIDE INJECTION.
TRANEXAMIC ACID IN SODIUM CHLORIDE injection, for intravenous use
Initial U.S. Approval: 1986

1 INDICATIONS AND USAGE

Tranexamic Acid in Sodium Chloride Injection is an antifibrinolytic indicated in patients with hemophilia for short-term use (two to eight days) to reduce or prevent hemorrhage and reduce the need for replacement therapy during and following tooth extraction (1).

2 DOSAGE AND ADMINISTRATION

- Before Extraction: Administer 10 mg/kg actual body weight of Tranexamic Acid in Sodium Chloride Injection intravenously with replacement therapy.
- After Extraction: Administer 10 mg/kg actual body weight 3-4 times daily for 2 to 8 days. Infuse no more than 10 mL/minute to avoid hypotension (2.1).
- Reduce the dosage for patients with renal impairment (2.2, 8.6).

3 DOSAGE FORMS AND STRENGTHS

Injection: 1,000 mg of tranexamic acid in 100 mL (10 mg/mL) sterile, unpreserved, colorless solution in a single-dose bag for intravenous use (3).

4 CONTRAINDICATIONS

- In patients with subarachnoid hemorrhage, due to risk of cerebral edemaand cerebral infarction (4).
- In patients with active intravascular clotting (4).
- In patients with severe hypersensitivity reactions to tranexamic acid or any of the ingredients (4).

5 WARNINGS AND PRECAUTIONS

- Risk of Thrombosis with concomitant use of Factor IX: Avoid concomitant use (5.1).
- Seizures: Inadvertent injection into neuraxial system may result in seizures (5.2).
- Hypersensitivity Reactions: In case of severe reaction, discontinue use seek immediate medical attention (5.3).
- Visual Disturbances: Visual or ocular adverse effects may occur. Discontinue use if visual or ocular symptoms occur (5.4).
- Dizziness may occur. Advise patients not to drive if dizziness occurs (5.5).

6 ADVERSE REACTIONS

Most common adverse reactions are nausea, vomiting, diarrhea, allergic dermatitis, giddiness, hypotension, and thromboembolic events (6).

To report SUSPECTED ADVERSE REACTIONS, contact [Enter Company Name] or FDA at 1-800-FDA-1088 or www.fda.gov/medwatch.

7 DRUG INTERACTIONS

- Prothrombotic Medical Products: Avoid concomitant use, can furtherincrease the risk of thromboembolic adverse reactions associated withtranexamic acid (5.1, 7.1, 8.3).
- Chlorpromazine: May result in increased risk of bleeding (7.2).

FULL PRESCRIBING INFORMATION

1 INDICATIONS AND USAGE

Tranexamic Acid in Sodium Chloride Injection is indicated in patients with hemophilia for short-term use (two to eight days) to reduce the risk of hemorrhage during and following tooth extraction.

2 DOSAGE AND ADMINISTRATION

2.1 Recommended Dosage

The recommended dose of Tranexamic Acid in Sodium Chloride Injection is 10 mg/kg actual body weight intravenously administered as a single dose, immediately before tooth extractions. Infuse no more than 10 mL/minute to avoid hypotension. Following tooth extraction, Tranexamic Acid in Sodium Chloride Injection may be administered for 2 to 8 days at a dose of 10 mg/kg actual body weight three to four times daily, intravenously.

Parenteral drug products should be inspected visually for particulate matter and discoloration prior to administration, whenever solution and container permit. Do not use Tranexamic Acid in Sodium Chloride Injection if particulate matter or coloration is seen.

Tranexamic Acid in Sodium Chloride Injection should NOT be mixed with blood. The drug is a synthetic amino acid and should NOT be mixed with solutions containing penicillin.

The premix flexible plastic container bag contains no preservative; discard any unused portion.

2.2 Recommended Dosage for Patients with Varying Degrees of Renal Impairment

The recommended dosage of Tranexamic Acid in Sodium Chloride Injection in patients with varying degrees of renal impairment is described in Table 1 [see Use in Specific Populations (8.6)].

Table 1. Recommended Dosage in Patients with Varying Degrees of Renal Impairment*

Serum Creatinine (mg/dL) | Tranexamic Acid in Sodium Chloride Injection Intravenous Dosage
1.36 to 2.83; (120 to 250 micromol/L) | 10 mg/kg twice daily
2.83 to 5.66; (250 to 500 micromol/L) | 10 mg/kg daily
>5.66; (>500 micromol/L) | 10 mg/kg every 48 hours or 5 mg/kg every 24 hours

*Dose reduction is recommended for all doses, both before and after tooth extraction.

3 DOSAGE FORMS AND STRENGTHS

Injection: 1,000 mg of tranexamic acid in 100 mL (10 mg/mL), colorless solution in a single-dose bag for intravenous use

4 CONTRAINDICATIONS

Tranexamic Acid in Sodium Chloride Injection is contraindicated:

- In patients with subarachnoid hemorrhage. Anecdotal experience indicates that cerebral edema and cerebral infarction may be caused by tranexamic acid in such patients.
- In patients with active intravascular clotting [see Warnings and Precautions (5.1)].
- In patients with history of hypersensitivity to tranexamic acid or any of the ingredients [see Warnings and Precautions (5.3)].

5 WARNINGS AND PRECAUTIONS

5.1 Thromboembolic Risk

Tranexamic Acid in Sodium Chloride Injection is contraindicated in patients with active intravascular clotting.

Tranexamic acid is an antifibrinolytic and may increase the risk of thromboembolic events. Venous and arterial thrombosis or thromboembolism has been reported in patients treated with tranexamic acid. Avoid concomitant use of Tranexamic Acid in Sodium Chloride Injection and medical products that are pro-thrombotic, as the risk of thrombosis may be increased. These medications include, but are not limited to, Factor IX Complex concentrates, Anti-inhibitor Coagulant concentrates, and hormonal contraceptives [see Drug Interactions (7.1) and Use in Specific Populations (8.3)].

5.2 Seizures

Tranexamic acid may cause seizures, including focal and generalized seizures. The most common setting for tranexamic acid-induced seizures has been during cardiovascular surgery (a setting in which Tranexamic Acid in Sodium Chloride Injection is not FDA approved and which uses doses of up to ten-fold higher than the recommended human dose and in patients inadvertently given tranexamic acid into the neuraxial system). Tranexamic Acid in Sodium Chloride Injection is not approved and not recommended for neuraxial administration. Consider dose reduction during surgery and dose adjustments for patients with clinical conditions such as renal dysfunction. Closely monitor the patient during surgery. Consider EEG monitoring for patients with history of seizures or who experience myoclonic movements, twitching, or show evidence of focal seizures. Discontinue Tranexamic Acid in Sodium Chloride Injection if seizures occur.

5.3 Hypersensitivity Reactions

Cases of hypersensitivity reactions, including anaphylactic reactions, have occurred with use of intravenous tranexamic acid. Discontinue treatment with Tranexamic Acid in Sodium Chloride Injection if serious reaction occurs, provide appropriate medical management, and do not restart treatment. Tranexamic Acid in Sodium Chloride Injection is contraindicated in patients with a history of hypersensitivity to tranexamic acid.

5.4 Visual Disturbances

Although not seen in humans, focal areas of retinal degeneration have been observed in cats, dogs and rats following oral or intravenous tranexamic acid at doses between 250 to 1600 mg/kg/day (6 to 40 times the recommended usual human dose) from 6 days to 1 year. No retinal changes have been observed in eye examinations of patients treated with tranexamic acid for up to 8 years. Patients expected to be treated for greater than 3 months may consider ophthalmic monitoring including visual acuity and optical coherence tomography at regular intervals. Discontinue Tranexamic Acid in Sodium Chloride Injection if changes in ophthalmological examination occurs.

5.5 Dizziness

Tranexamic acid may cause dizziness. Concomitant use of other drugs that may also cause dizziness may worsen this effect. Advise patients to avoid driving or using machines until they know how Tranexamic Acid in Sodium Chloride Injection affects them.

6 ADVERSE REACTIONS

The following clinically significant adverse reactions are described elsewhere in the labeling:

- Thromboembolic Risk [see Warnings and Precautions (5.1)]
- Seizures [see Warnings and Precautions (5.2)]
- Hypersensitivity Reactions [see Warnings and Precautions (5.3)]
- Visual Disturbances [see Warnings and Precautions (5.4)]
- Dizziness [see Warnings and Precautions (5.5)]

6.1 Postmarketing Experience

The following adverse reactions have been identified during postapproval use of tranexamic acid. Because these reactions are reported voluntarily from a population of uncertain size, it is not always possible to reliably estimate their frequency or establish a causal relationship to drug exposure.

Gastrointestinal disturbances (nausea, vomiting, diarrhea) may occur and may resolve with dose-reduction. Allergic dermatitis and giddiness have been reported. Hypotension has been reported when intravenous injection is too rapid.

Thromboembolic events (e.g., deep vein thrombosis, pulmonary embolism, cerebral thrombosis, acute renal cortical necrosis, and central retinal artery, vein obstruction and cases associated with concomitant use of combination hormonal contraceptives) have been rarely reported in patients receiving tranexamic acid for indications other than hemorrhage prevention in patients with hemophilia. Convulsion, cromatopsia, and visual impairment have also been reported.

Anaphylaxis or anaphylactoid reactions have been reported that are suggestive of a causal relationship.

7 DRUG INTERACTIONS

7.1 Prothrombotic Medical Products

Avoid concomitant use of Tranexamic Acid in Sodium Chloride Injection with medical products that are prothrombotic because concomitant use can further increase the risk of thromboembolic adverse reactions associated with tranexamic acid [see Warnings and Precautions (5.1) and Use in Specific Populations (8.3)].

7.2 Chlorpromazine

Concurrent use of chlorpromazine and Tranexamic Acid in Sodium Chloride Injectionmay result in increased risk of bleeding.

8 USE IN SPECIFIC POPULATIONS

8.1 Pregnancy

Risk Summary

Available data from published studies, case series and case reports with tranexamic acid use in pregnant women in the second and third trimester and at the time of delivery have not identified a drug-associated risk of miscarriage or adverse maternal or fetal outcomes. There are no reports regarding the use of tranexamic acid during the first trimester of pregnancy; therefore, there are no data regarding the risk of major birth defects with use of tranexamic acid during pregnancy. However, tranexamic acid is known to pass the placenta and appears in cord blood at concentrations approximately equal to maternal concentration (see Data). Reproduction studies performed in mice, rats, and rabbits have not revealed any adverse effects on the fetus due to tranexamic acid.

The estimated background risk for major birth defects and miscarriage for the indicated population is unknown. All pregnancies have a background risk of birth defect, loss, or other adverse outcomes. In the U.S. general population, the estimated background risk of major birth defects and miscarriage in the clinically recognized pregnancies is 2-4% and 15−20%, respectively.

Data

Human Data

Tranexamic acid passes through the placenta. The concentration in cord blood after an intravenous injection of 10 mg/ kg to pregnant women is about 30 mg/liter, as high as in the maternal blood.

8.2 Lactation

Risk Summary

Published literature reports the presence of tranexamic acid in human milk. There are no data on the effects of tranexamic acid on the breastfed child or the effects on milk production. The developmental and health benefits of breastfeeding should be considered along with the mother’s clinical need for Tranexamic Acid in Sodium Chloride Injection and any potential adverse effects on the breastfed child from Tranexamic Acid in Sodium Chloride Injection or from the underlying maternal condition.

8.3 Females and Males of Reproductive Potential

Contraception

Concomitant use of Tranexamic Acid in Sodium Chloride Injection, which is an antifibrinolytic, with hormonal contraceptives may increase the risk for thromboembolic adverse reactions. Advise patients to use an effective alternative (nonhormonal) contraceptive method [see Warnings and Precautions (5.5) and Drug Interactions (7.1)].

8.4 Pediatric Use

There are limited data concerning the use of tranexamic acid in pediatric patients with hemophilia who are undergoing tooth extraction. The limited data suggest that there are no significant pharmacokinetic differences between adult and pediatric patients.

8.5 Geriatric Use

Clinical studies of tranexamic acid did not include sufficient numbers of subjects aged 65 and over to determine whether they respond differently from younger subjects. Other reported clinical experience has not identified differences in responses between the elderly and younger patients.

This drug is known to be substantially excreted by the kidney, and the risk of toxic reactions to this drug may be greater in patients with impaired renal function. Because elderly patients are more likely to have decreased renal function, care should be taken in dose selection, and it may be useful to monitor renal function [Dosage and Administration (2.2) and Clinical Pharmacology (12.3)].

8.6 Renal Impairment

Reduce the dosage of Tranexamic Acid in Sodium Chloride Injection in patients with renal impairment, based on the patient’s serum creatinine [see Dosage and Administration (2.2) and Clinical Pharmacology (12.3)].

10 OVERDOSAGE

Cases of overdosage of tranexamic acid have been reported. Based on these reports, symptoms of overdosage may be gastrointestinal, e.g, nausea, vomiting, diarrhea; hypotensive, e.g, orthostatic symptoms; thromboembolic; e.g, arterial, venous, embolic; visual impairment; mental status changes; myoclonus and rash. Tranexamic acid is not dialyzable.

11 DESCRIPTION

Tranexamic acid is trans-4-(aminomethyl)cyclohexanecarboxylic acid, an antifibrinolytic agent. Tranexamic acid is a white crystalline powder. The structural formula is

Empirical Formula: C8H15NO2 Molecular Weight: 157.2

Tranexamic Acid in Sodium Chloride Injection is a clear to colorless sterile, nonpyrogenic injectable solution for intravenous administration. Each IV bag contains 1000 mg tranexamic acid, USP, 700 mg of sodium chloride, USP and Water for Injection, USP. The aqueous solution has a pH of 6.5 to 8.0.

12 CLINICAL PHARMACOLOGY

12.1 Mechanism of Action

Tranexamic acid is a synthetic lysine amino acid derivative, which diminishes the dissolution of hemostatic fibrin by plasmin. In the presence of tranexamic acid, the lysine receptor binding sites of plasmin for fibrin are occupied, preventing binding to fibrin monomers, thus preserving and stabilizing fibrin’s matrix structure.

The antifibrinolytic effects of tranexamic acid are mediated by reversible interactions at multiple binding sites within plasminogen. Native human plasminogen contains 4 to 5 lysine binding sites with low affinity for tranexamic acid (Kd = 750 μmol/l) and 1 with high affinity (Kd = 1.1 μmol/L). The high affinity lysine site of plasminogen is involved in its binding to fibrin. Saturation of the high affinity binding site with tranexamic acid displaces plasminogen from the surface of fibrin. Although plasmin may be formed by conformational changes in plasminogen, binding to and dissolution of the fibrin matrix is inhibited.

12.2 Pharmacodynamics

Tranexamic acid in concentrations of 1 mg/mL and 10 mg/mL prolongs the thrombin time. An antifibrinolytic concentration of tranexamic acid remains in different tissues for about 17 hours, and in the serum, up to seven or eight hours.

Tranexamic acid in concentrations up to 10 mg/mL blood has no influence on the platelet count, the coagulation time or various coagulation factors in whole blood or citrated blood from healthy subjects.

12.3 Pharmacokinetics

Distribution

The initial volume of distribution is about 9 to 12 liters. The plasma protein binding of tranexamic acid is about 3% at therapeutic plasma levels and seems to be fully accounted for by its binding to plasminogen. Tranexamic acid does not bind to serum albumin.

Elimination

After an intravenous dose of 1 g, the plasma concentration time curve shows a triexponential decay with a half-life of about 2 hours for the terminal elimination phase.

Excretion

Urinary excretion is the main route of elimination via glomerular filtration. Overall renal clearance is equal to overall plasma clearance (110 to 116 mL/min) and more than 95% of the dose is excreted in the urine as the unchanged drug. Excretion of tranexamic acid is about 90% at 24 hours after intravenous administration of 10 mg/kg body weight.

Specific Populations

Renal Impairment

The effect of renal impairment on the disposition of Tranexamic Acid in Sodium Chloride Injection has not been evaluated. Urinary excretion following a single intravenous injection of tranexamic acid declines as renal function decreases. Following a single 10 mg/kg intravenous injection of tranexamic acid, the 24-hour urinary fractions of tranexamic acid with serum creatinine concentrations 1.4 – 2.8, 2.8 – 5.7, and greater than 5.7 mg/dL were 51, 39, and 19%, respectively. The 24-hour tranexamic acid plasma concentrations for these patients demonstrated a direct relationship to the degree of renal impairment. Therefore, dose adjustment is needed in patients with renal impairment [see Dosage and Administration (2.2) and Use in Specific Populations (8.6)].

Drug Interaction Studies

No studies of interactions between Tranexamic Acid in Sodium Chloride Injection and other drugs have been conducted.

13 NONCLINICAL TOXICOLOGY

13.1 Carcinogenesis, Mutagenesis, Impairment of Fertility

An increased incidence of leukemia in male mice receiving tranexamic acid in food at a concentration of 4.8% (equivalent to doses as high as 5 g/kg/day) may have been related to treatment. Female mice were not included in this experiment.

Hyperplasia of the biliary tract and cholangioma and adenocarcinoma of the intrahepatic biliary system have been reported in one strain of rats after dietary administration of doses exceeding the maximum tolerated dose for 22 months. Hyperplastic, but not neoplastic, lesions were reported at lower doses. Subsequent long-term dietary administration studies in a different strain of rat, each with an exposure level equal to the maximum level employed in the earlier experiment, have failed to show such hyperplastic/neoplastic changes in the liver. No mutagenic activity has been demonstrated in several in vitro and in vivo test systems.

16 HOW SUPPLIED/STORAGE AND HANDLING

Tranexamic Acid in Sodium Chloride Injection is supplied as a sterile, unpreserved, colorless solution in a single-dose polymeric bag containing 1000 mg tranexamic acid in 100 mL of solution (10 mg/mL) sealed with a Twist Off port and oversealed in an aluminum pouch (NDC 51754-0108-1).

Discard any unused portion.

Store at 20°C to 25°C (68°F to 77°F); excursions permitted to 15°C to 30°C (59°F to 86°F) [see USP Controlled Room Temperature].

Manufactured and Distributed by:

Exela Pharma Sciences, LLC

1245 Blowing Rock Blvd

Lenoir, NC 28645

17 PATIENT COUNSELING INFORMATION

Thromboembolic Risk

- Inform patients that Tranexamic Acid in Sodium Chloride Injection may cause venous and arterial thrombosis or thromboembolism and to contact their healthcare provider for any signs or symptoms suggestive of thromboembolism.
- Advise patients using hormonal contraception that combined use with Tranexamic Acid in Sodium Chloride Injection may increase the risk for thromboembolic adverse reactions and to use effective alternative (nonhormonal) contraception during therapy with Tranexamic Acid in Sodium Chloride Injection [see Warnings and Precautions (5.1), Drug Interactions (7.1) and Use in Specific Populations (8.3)].

Seizures

Inform patients that Tranexamic Acid in Sodium Chloride Injection may cause seizures and to contact their healthcare provider for any signs or symptoms suggestive of seizures [see Warnings and Precautions (5.2)].

Hypersensitivity Reactions

Inform patients that Tranexamic Acid in Sodium Chloride Injection may cause hypersensitivity reactions and to contact their healthcare provider for any signs or symptoms of hypersensitivity reactions [see Warnings and Precautions (5.3)].

Visual Disturbances

Inform patients that Tranexamic Acid in Sodium Chloride Injection can cause visual disturbance and that they should report any eye symptoms or change in their vision to their healthcare provider and to follow-up with an ophthalmologist for a complete ophthalmologic evaluation, including dilated retinal examination of the retina [see Warnings and Precautions (5.4)].

Risk of Driving and Operating Machinery

Inform patients that Tranexamic Acid in Sodium Chloride Injectionmay cause dizziness, and that the patient should be cautioned about driving, operating machinery, or performing hazardous tasks while taking Tranexamic Acid in Sodium Chloride Injection [see Warnings and Precautions (5.5)].

PACKAGE/LABEL PRINCIPAL DISPLAY PANEL

NDC 51754-0108-1 100 mL

Tranexamic Acid Premixed Injection

1000 mg per 100 mL (10 mg per mL)

Single-dose for intravenous use only Discard unused portion of drug

Each mL contains 10 mg of Tranexamic Acid, USP, 7 mg of Sodium Chloride USP in Water for Injection, USP. pH 6.5-8.0.

DOSAGE: See package insert for complete information on dosage and administration.

CAUTIONS: Check for minute leaksby squeezing bag firmly. Do not use unless solution is clear. Do not add supplemental medication. Must not be used in series connections.

STORAGE: Store at 20°C to 25°C (68°F to 77°F); excursions permitted to 15°C to 30°C (59°F to 86°F).

Exela

Mfg. and Dist. By: Exela Pharma Sceinces, LLC, USA